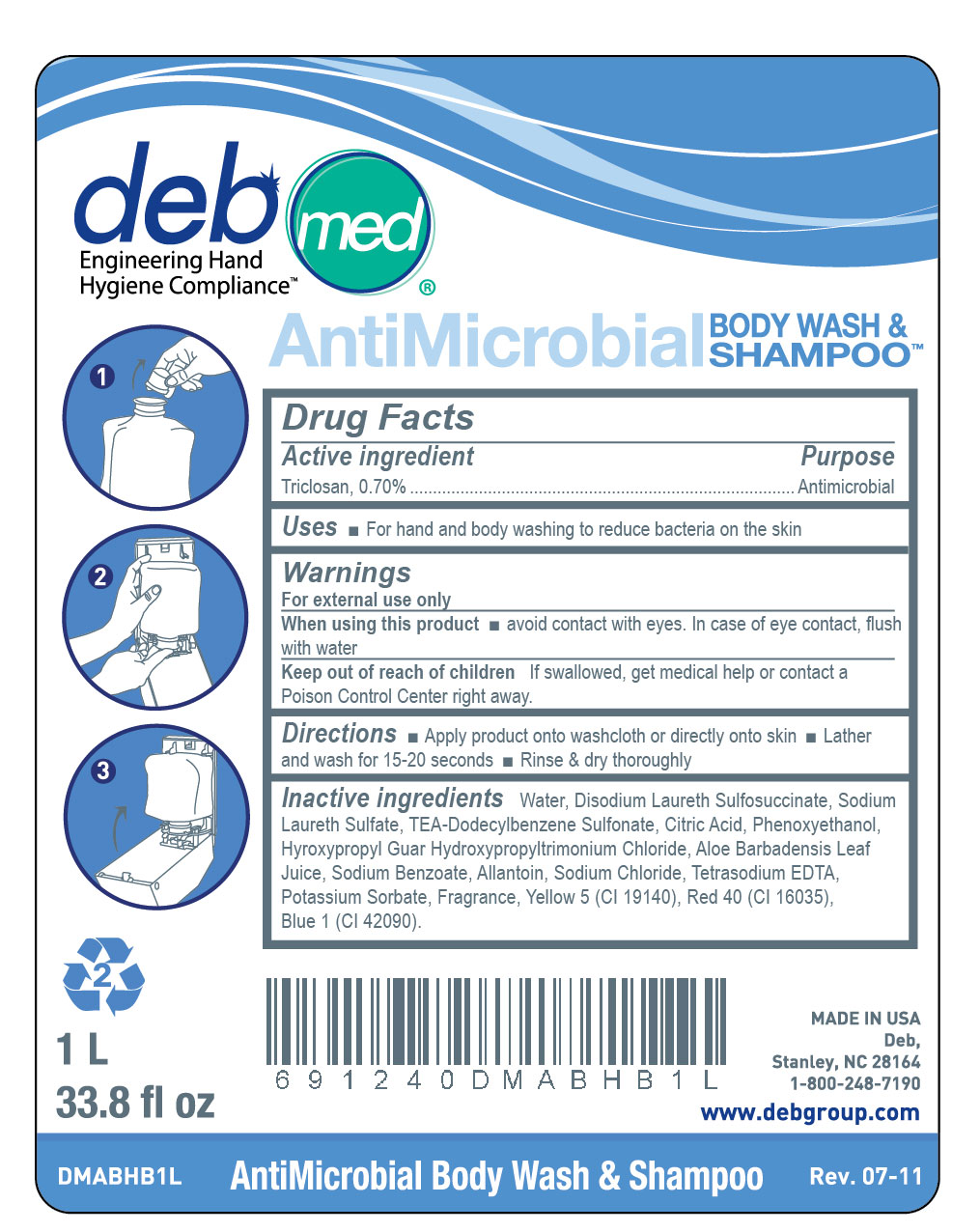 DRUG LABEL: DebMed Antimicrobial Body Wash and Shampoo
NDC: 11084-061 | Form: LIQUID
Manufacturer: Deb USA, Inc.
Category: otc | Type: HUMAN OTC DRUG LABEL
Date: 20110719

ACTIVE INGREDIENTS: Triclosan 0.70 mL/100 mL
INACTIVE INGREDIENTS: WATER; DISODIUM LAURETH SULFOSUCCINATE; TEA-DODECYLBENZENESULFONATE; SODIUM LAURETH SULFATE; ANHYDROUS CITRIC ACID ; PHENOXYETHANOL; SODIUM CHLORIDE; EDETATE SODIUM; ALOE VERA LEAF; GUAR GUM; ALLANTOIN; FD&C RED NO. 40; FD&C YELLOW NO. 5  ; SODIUM BENZOATE; POTASSIUM SORBATE; FD&C BLUE NO. 1

Drug Facts

Active ingredient

Triclosan, 0.70%

Purpose

Antimicrobial

Uses

For hand and body washing to reduce bacteria on the skin

Warnings

For external use only

When using this product avoid contact with eyes. In case of eye contact, flush with water

Keep out of reach of children

If swallowed, get medical help or contact a Poison Control Center right away.

Directions

Apply product onto washcloth or directly onto skin

Lather and wash for 15-20 seconds

Rinse and dry thoroughly

Inactive ingredients

Water, Disodium Laureth Sulfosuccinate, Sodium Laureth Sulfate, TEA-Dodecylbenzene Sulfonate, Citric Acid, Phenoxyethanol, Hyroxypropyl Guar Hydroxypropyltrimonium Chloride, Aloe Barbadensis Leaf Juice, Sodium Benzoate, Allantoin, Sodium Chloride, Tetrasodium EDTA, Potassium Sorbate, Fragrance, Yellow 5 (CI19140), Red 40 (CI 16035), Blue 1 (CI 42090).

PACKAGE LABEL

DebMed Engineering Hand Hygiene Compliance

AntiMicrobial Body Wash and Shampoo

1L

33.8 fl oz

Made in USA

DMABHB1L